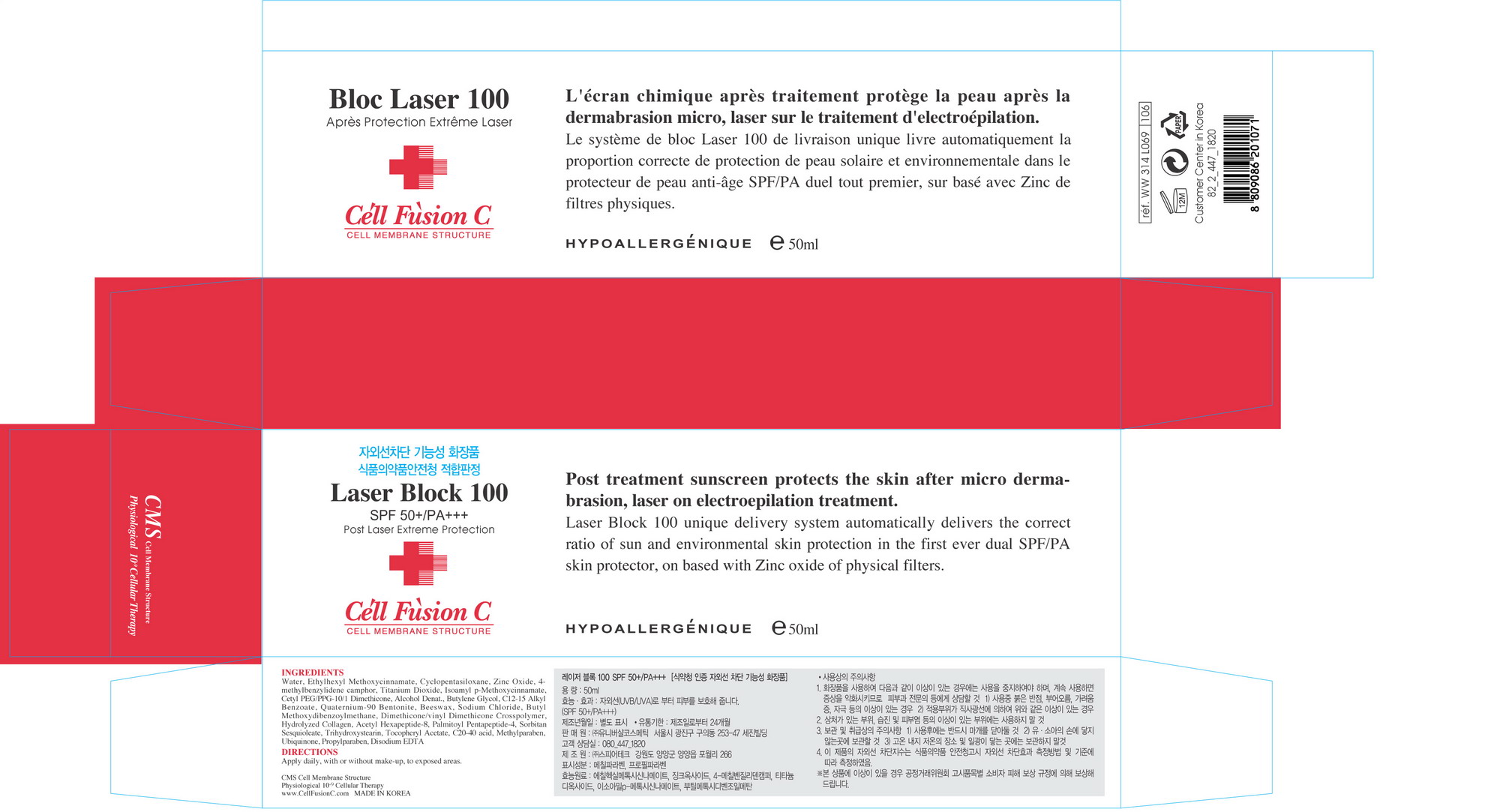 DRUG LABEL: Laser Block 100
NDC: 52554-3001 | Form: CREAM
Manufacturer: Universal Cosmetic Co., Ltd
Category: otc | Type: HUMAN OTC DRUG LABEL
Date: 20100804

ACTIVE INGREDIENTS: OCTINOXATE 0.07 mL/1 mL; ZINC OXIDE 0.05 mL/1 mL; ENZACAMENE 0.03 mL/1 mL; TITANIUM DIOXIDE 0.02 mL/1 mL; AMILOXATE 0.02 mL/1 mL; AVOBENZONE 0.005 mL/1 mL

Drug Facts

ACTIVE INGREDIENT

Active ingredients: Ethylhexyl Methoxycinnamate, Zinc Oxide, 4-Methylbenzylidene camphor, Titanium Dioxide, Isoamyl p-Methoxycinnamate, Butyl Methoxydibenzoylmethane

Uses
■ Perfectly blocks UV rays without stimuli
■ Effective against
l PIH(Post Inflammatory Pigmentation)
l Photosensitive skins
l DNA destruction
■ Suitable for skin that underwent medical treatment
■ Helps keep moisturize
Warning
For external use only
When using this product
■ Avoid eye area. If contact occurs, rinse eyes thoroughly
■ If following abnormal symptoms occurs after use, stop use and ask doctor
l red specks, swelling, itching
Keep out of reach of the children
Direction
■ Before finishing skincare, rub a proper quantity over the whole face that underwent IPL or Laser therapy.
Other Information
■ store between 20-25 °C (68-77 °F)
■ avoid freezing and excessive heat above 40 °C (104 °F)
■ close cap after use.